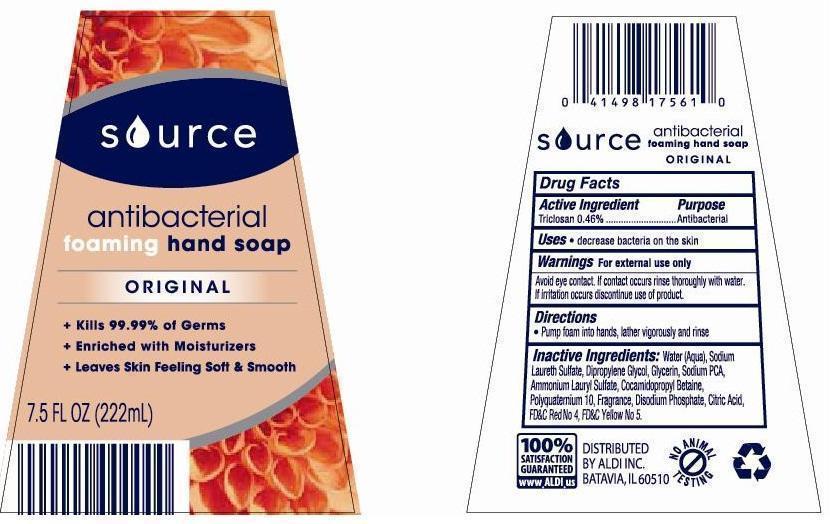 DRUG LABEL: Source Antibacterial Foaming Hand Original
NDC: 64024-100 | Form: LIQUID
Manufacturer: Aldi Inc.
Category: otc | Type: HUMAN OTC DRUG LABEL
Date: 20130221

ACTIVE INGREDIENTS: TRICLOSAN 0.46 mg/1 mL
INACTIVE INGREDIENTS: Water; SODIUM LAURETH SULFATE; DIPROPYLENE GLYCOL; glycerin; AMMONIUM LAURYL SULFATE; COCAMIDOPROPYL BETAINE; POLYQUATERNIUM-10 (400 CPS AT 2%); FD&C RED NO. 4; FD&C YELLOW NO. 5

Drug Fact

Active Ingredient Purpose
Triciosan 0.46% ********** Antibecterial

PURPOSE

Decreases bacteria on the skin

KEEP OUT OF REACH OF CHILDREN

avoid eye contact, if contact occurs rinse thoroughly with water.

INDICATIONS AND USAGE

Pump foam into hands, lather vigorously and rinse

WARNINGS

For external use only.
avoid eye contact, if contact occurs rinse thoroughly with water. If irritation occurs discontinue use of product.

DOSAGE AND ADMINISTRATION

Pump foam into hands, lather vigorously and rinse.

INACTIVE INGREDIENT

Water, Sodium Laureth Sulfate, Dipropylene Glycol, Glycerin, Sodium PCA, Ammonium Lauryl Sulfate, Cocamidopropyl Betaire, Polyquaterium 10, Fragrance, Disodium Phosphate, Citric Acid, FD&C Red No. 4, FD&C Yellow No. 5